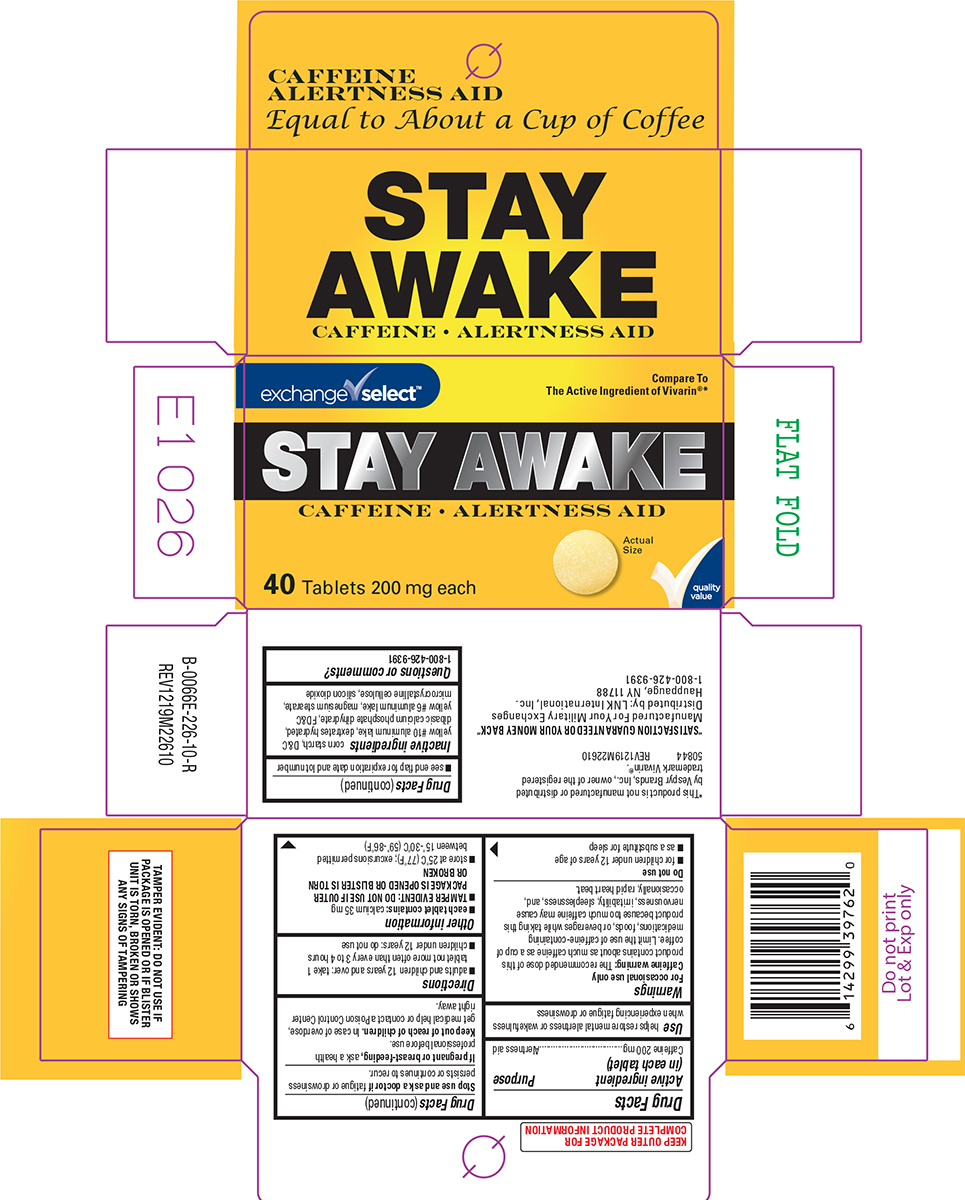 DRUG LABEL: Stay Awake
NDC: 55301-226 | Form: TABLET
Manufacturer: ARMY AND AIR FORCE EXCHANGE SERVICE
Category: otc | Type: HUMAN OTC DRUG LABEL
Date: 20260106

ACTIVE INGREDIENTS: CAFFEINE 200 mg/1 1
INACTIVE INGREDIENTS: STARCH, CORN; D&C YELLOW NO. 10 ALUMINUM LAKE; DEXTROSE MONOHYDRATE; DIBASIC CALCIUM PHOSPHATE DIHYDRATE; FD&C YELLOW NO. 6 ALUMINUM LAKE; MAGNESIUM STEARATE; MICROCRYSTALLINE CELLULOSE; SILICON DIOXIDE

Exchange Select 44-226

Active ingredient (in each tablet)

Caffeine 200 mg

Purpose

Alertness aid

Use

helps restore mental alertness or wakefulness when experiencing fatigue or drowsiness

Warnings

For occasional use only

Caffeine warning: The recommended dose of this product contains about as much caffeine as a cup of coffee. Limit the use of caffeine-containing medications, foods, or beverages while taking this product because too much caffeine may cause nervousness, irritability, sleeplessness, and, occasionally, rapid heart beat.

Do not use

- for children under 12 years of age
- as a substitute for sleep

Stop use and ask a doctor if

fatigue or drowsiness persists or continues to recur.

If pregnant or breast-feeding,

ask a health professional before use.

Keep out of reach of children.

In case of overdose, get medical help or contact a Poison Control Center right away.

Directions

- adults and children 12 years and over: take 1 tablet not more often than every 3 to 4 hours
- children under 12 years: do not use

Other information

- each tablet contains: calcium 35 mg
- TAMPER EVIDENT: DO NOT USE IF OUTER PACKAGE IS OPENED OR BLISTER IS TORN OR BROKEN
- store at 25ºC (77ºF); excursions permitted between 15º-30ºC (59º-86ºF)
- see end flap for expiration date and lot number

Inactive ingredients

corn starch, D&C yellow #10 aluminum lake, dextrates hydrated, dibasic calcium phosphate dihydrate, FD&C yellow #6 aluminum lake, magnesium stearate, microcrystalline cellulose, silicon dioxide

Questions or comments?

1-800-426-9391

Principal Display Panel

exchange✓select™

Compare To
The Active Ingredient of Vivarin®*

STAY AWAKE
CAFFEINE • ALERTNESS AID

40 Tablets 200 mg each

Actual
Size

✓quality
value

CAFFEINE
ALERTNESS AID
Equal to About a Cup of Coffee

TAMPER EVIDENT: DO NOT USE IF
PACKAGE IS OPENED OR IF BLISTER
UNIT IS TORN, BROKEN OR SHOWS
ANY SIGNS OF TAMPERING

*This product is not manufactured or distributed
by Vespyr Brands, Inc., owner of the registered
trademark Vivarin®.
50844 REV1219M22610

"SATISFACTION GUARANTEED OR YOUR MONEY BACK"
Manufactured For Your Military Exchanges
Distributed by: LNK International, Inc.
Hauppauge, NY 11788
1-800-426-9391

Exchange Select 44-226